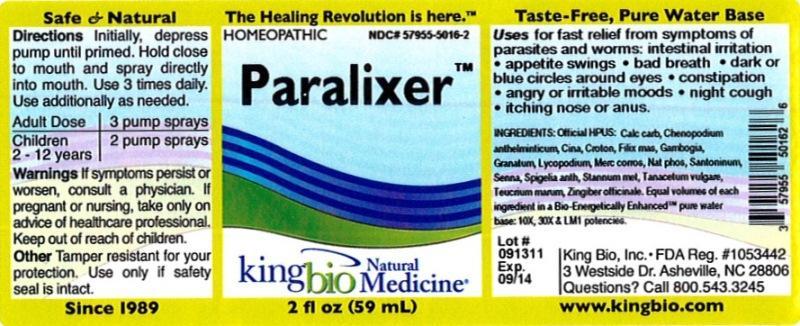 DRUG LABEL: Paralixer
NDC: 57955-5016 | Form: LIQUID
Manufacturer: King Bio Inc.
Category: homeopathic | Type: HUMAN OTC DRUG LABEL
Date: 20120918

ACTIVE INGREDIENTS: OYSTER SHELL CALCIUM CARBONATE, CRUDE 10 [hp_X]/59 mL; DYSPHANIA AMBROSIOIDES 10 [hp_X]/59 mL; ARTEMISIA CINA PRE-FLOWERING TOP 10 [hp_X]/59 mL; CROTON TIGLIUM SEED 10 [hp_X]/59 mL; DRYOPTERIS FILIX-MAS ROOT 10 [hp_X]/59 mL; GAMBOGE 10 [hp_X]/59 mL; PUNICA GRANATUM ROOT BARK 10 [hp_X]/59 mL; LYCOPODIUM CLAVATUM SPORE 10 [hp_X]/59 mL; MERCURIC CHLORIDE 10 [hp_X]/59 mL; SODIUM PHOSPHATE, DIBASIC, HEPTAHYDRATE 10 [hp_X]/59 mL; SANTONIN 10 [hp_X]/59 mL; SENNA LEAF 10 [hp_X]/59 mL; SPIGELIA ANTHELMIA 10 [hp_X]/59 mL; TIN 10 [hp_X]/59 mL; TANACETUM VULGARE TOP 10 [hp_X]/59 mL; TEUCRIUM MARUM 10 [hp_X]/59 mL; GINGER 10 [hp_X]/59 mL
INACTIVE INGREDIENTS: WATER

Paralixer

Active Ingredients

Official HPUS: Calcarea carbonica, Chenopodium anthelminticum, Cina, Croton tiglium, Filix mas, Gambogia, Granatum, Lycopodium clavatum, Mercurius corrosivus, Natrum phosphoricum, Santoninum, Senna, Spigelia anthelmia, Stannum metallicum, Tanacetum vulgare, Teucrium marum and Zingiber officinale.

Inactive Ingredient

Equal volumes of each ingredient in a Bio-Energetically Enhanced pure water base: 10X, 30X and LM1 potencies.

Purpose

Uses for fast relief from symptoms of parasites and worms:

- intestinal irritation
- appetite swings
- bad breath
- dark or blue circles around eyes
- constipation
- angry or irritable moods
- night cough
- itching nose or anus

Dosage and Administration

Directions: Initially, depress pump until primed. Hold close to mouth and spray directly into mouth. Use 3 times daily. Use additionally as needed.

Adult Dose 3 pump sprays

Children 2 - 12 years 2 pump sprays

Warnings

If symptoms persist or worsen, consult a physician. If pregnant or nursing, take only on advice of healthcare professional. Keep out of reach of children.

Other: Tamper resistant for your protection. Use only if safety seal is intact.

Keep out of reach of children.

Indications and Usage

Uses for fast relief from symptoms of parasites and worms: intestinal irritation, appetite swings, bad breath, dark or blue circles around eyes, constipation, angry or irritable moods, night cough, itching nose or anus.

PACKAGE LABEL

King Bio Inc.

3 Westside Drive

Asheville, NC 28806

Questions? Call 800.543.3245

www.kingbio.com